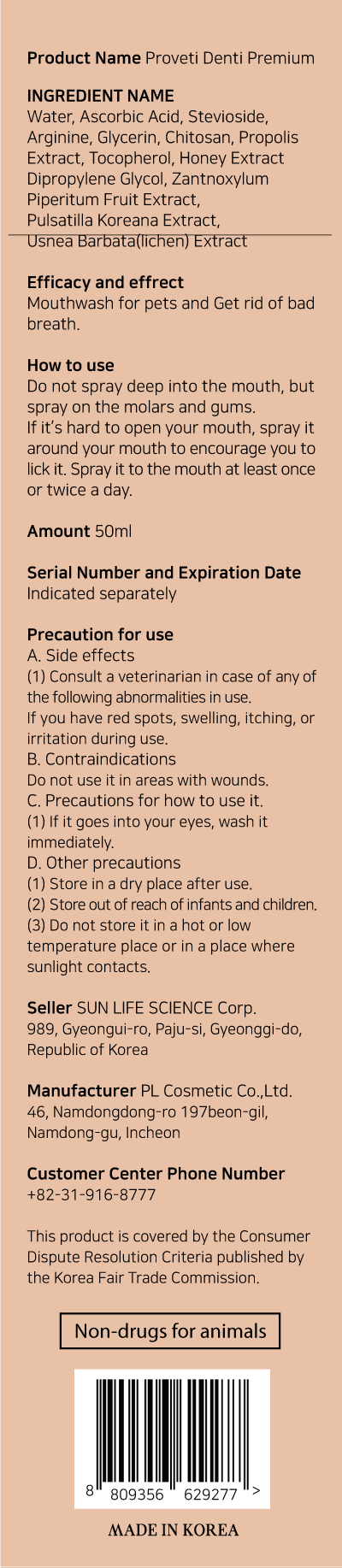 DRUG LABEL: PROVETI DENTI PREMIUM
NDC: 86157-0001 | Form: LIQUID
Manufacturer: SUN LIFE SCIENCE Co.,Ltd.
Category: animal | Type: OTC ANIMAL DRUG LABEL
Date: 20220308

ACTIVE INGREDIENTS: POLIGLUSAM 1 g/100 mL; PROPOLIS WAX 0.1 g/100 mL
INACTIVE INGREDIENTS: WATER

ACTIVE INGREDIENT

Chitosan(Poliglusam), Propolis Wax(Extract)

INACTIVE INGREDIENT

water, ascorbic acid, stevioside, arginine, glycerin, tocopherol, dipropylene glycol, zantnoxylum piperitum fruit extract, pulsatilla koreana extract, usnea barbata (lichen) extract

PURPOSE

Mouthwash for pets and Get rid of bad breath.

Keep out of reach of children

INDICATIONS AND USAGE

Do not spray deep into the mouth, but spray on the molars and gums.

If it's hard to open your mouth, spray it around your mouth to encourage you to lick it.

Spray it to the mouth at least once or twice a day.

WARNINGS

A. Side effects
(1) Consult a veterinarian in case of any of the following abnormalities in use.If you have red spots, swelling, itching, or irritation during use.

B. Contraindications
Do not use it in areas with wounds.

C. Precautions for how to use it.
(1) If it goes into your eyes, wash it immediately.

D. Other precautions
(1) Store in a dry place after use.
(2) Store out of reach of infants and children.
(3) Do not store it in a hot or low temperature place or in a place where sunlight contacts.

DOSAGE AND ADMINISTRATION

For external use only